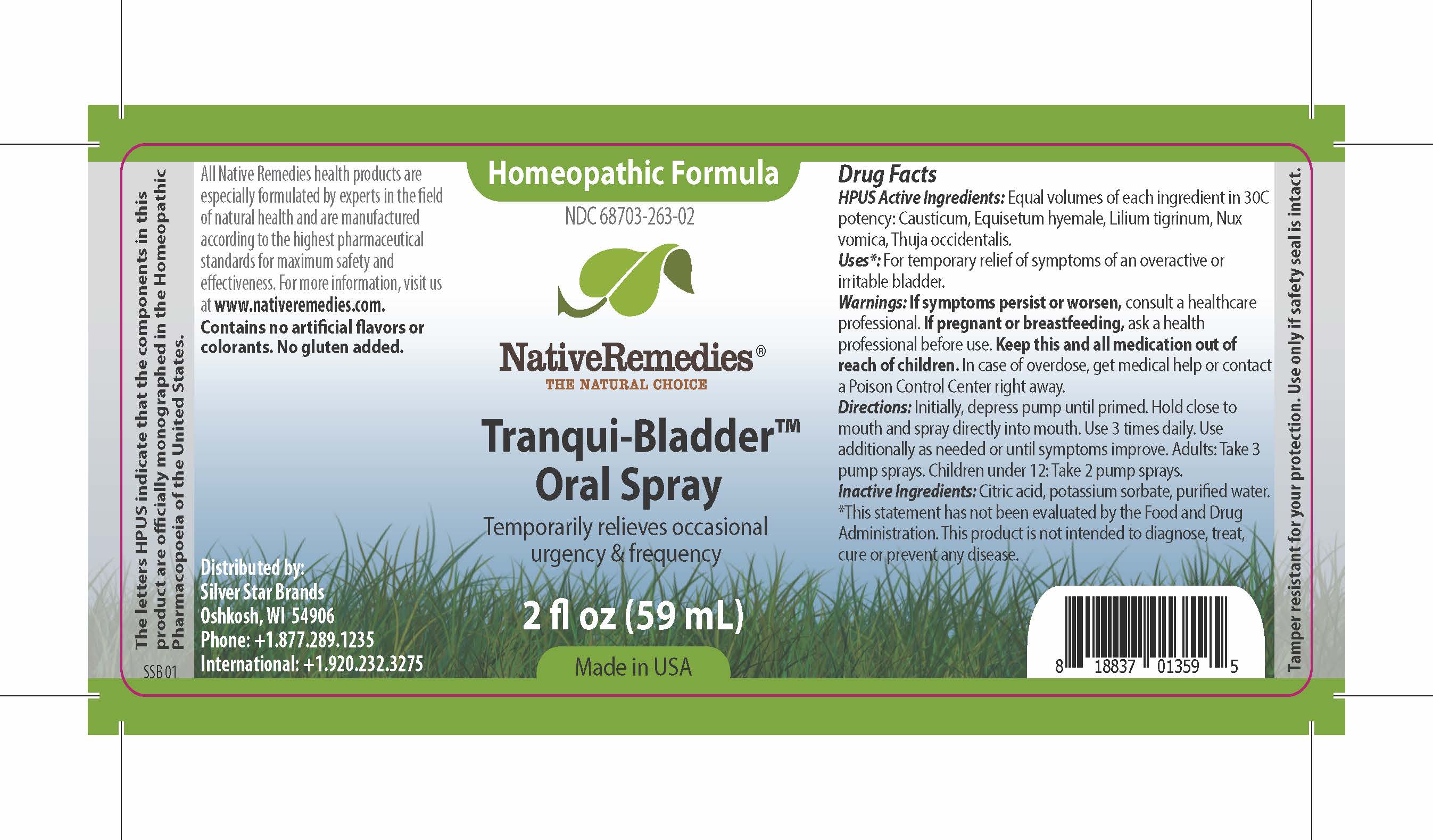 DRUG LABEL: Tranqui-Bladder
NDC: 68703-263 | Form: SPRAY
Manufacturer: Silver Star Brands
Category: homeopathic | Type: HUMAN OTC DRUG LABEL
Date: 20161018

ACTIVE INGREDIENTS: LILIUM LANCIFOLIUM WHOLE 30 [hp_C]/59 mL; STRYCHNOS NUX-VOMICA WHOLE 30 [hp_C]/59 mL; THUJA OCCIDENTALIS WHOLE 30 [hp_C]/59 mL; EQUISETUM HYEMALE 30 [hp_C]/59 mL; CAUSTICUM 30 [hp_C]/59 mL
INACTIVE INGREDIENTS: ANHYDROUS CITRIC ACID; POTASSIUM SORBATE; WATER

NativeRemedies® Tranqui-Bladder™ Oral Spray

HPUS Active Ingredients:

Equal volumes of each ingredient in 30C potency: Causticum hyemale, Lilium tigrinum, Nux vomica, Thuja occidentalis.

Uses*:

For temporary relief of symptoms of an overactive or irritable bladder.

*This statement has not been evaluated by the Food and Drug Administration. This product is not intended to diagnose, treat, cure or prevent any disease.

Warnings:

If symptoms persist or worsen, consult a healthcare professional. If pregnant or breastfeeding, ask a health professional before use. Keep this and all medication out of reach of children. In case of overdose, get medical help or contact a Poison Control Center right away.

Directions:

Initially, depress pump until primed. Hold close to mouth and spray directly into mouth. Use 3 time daily. Use additionally as needed or until symptoms improve. Adults: Take 3 pump sprays. Children under 12: Take 2 pump sprays.

OTHER SAFETY INFORMATION

All Native Remedies health products are especially formulated by experts in the field of natural health and are manufactured according to the highest pharmaceutical standards for maximum safety and effectiveness. For mroe information, visit us at www.nativeremedies.com

Contains no artificial flavors or colorants. No gluten added.

Inactive Ingredients:

Citric acid, potassium sorbate, purified water.

KEEP OUT OF REACH OF CHILDREN

Keep this and all medication out of reach of children. In case of overdose, get medical help or contact a Poison Control Center right away.

PREGNANCY OR BREAST FEEDING

If pregnant or breastfeeding, ask a health professional before use.

PURPOSE

Temporarily relieves occasional urgency & frequency